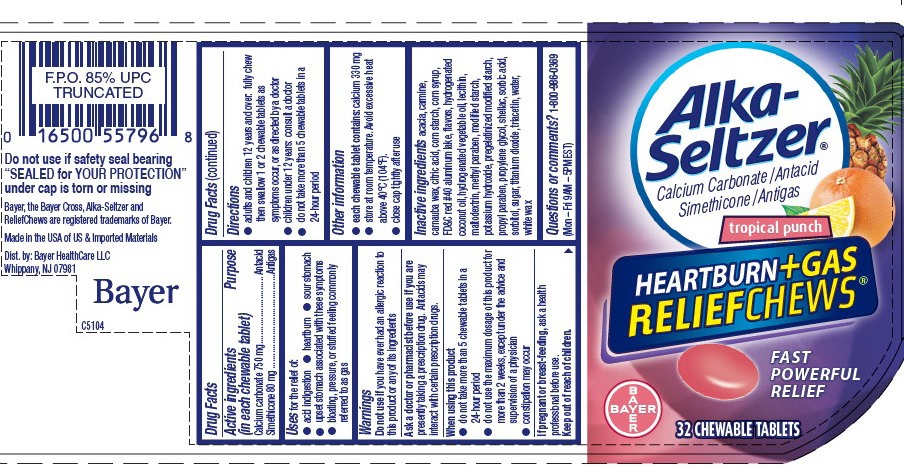 DRUG LABEL: Alka-Seltzer Heartburn Plus Gas ReliefChews Tropical Punch
NDC: 0280-0225 | Form: TABLET, CHEWABLE
Manufacturer: Bayer HealthCare LLC.
Category: otc | Type: HUMAN OTC DRUG LABEL
Date: 20251204

ACTIVE INGREDIENTS: DIMETHICONE 80 mg/1 1; CALCIUM CARBONATE 750 mg/1 1
INACTIVE INGREDIENTS: ACACIA; CARNAUBA WAX; MODIFIED CORN STARCH (1-OCTENYL SUCCINIC ANHYDRIDE); CORN SYRUP; POTASSIUM HYDROXIDE; FD&C RED NO. 40; HYDROGENATED COCONUT OIL; MALTODEXTRIN; METHYLPARABEN; PROPYLPARABEN; SORBIC ACID; SORBITOL; TITANIUM DIOXIDE; TRIACETIN; WATER; WHITE WAX; SHELLAC

Alka-Seltzer® Heartburn + Gas ReliefChews™ Tropical Punch

Drug Facts

ACTIVE INGREDIENT

Active ingredient (in each chewable tablet) | Purpose
Calcium carbonate 750 mg | Antacid
Simethicone 80 mg | Antigas

Uses

for the relief of:

- acid indigestion
- heartburn
- sour stomach
- upset stomach associated with these symptoms
- bloating, pressure, or stuffed feeling commonly referred to as gas

Warnings

Do not use if you have ever had an allergic reaction to this product or any of its ingredients

Ask a doctor or pharmacist before use if you are presently taking a prescription drug. Antacids may interact with certain prescription drugs.

When using this product

- do not take more than 6 chewable tablets in a 24-hour period
- do not use the maximum dosage of this product for more than 2 weeks, except under the advice and supervision of a physician
- constipation may occur

PREGNANCY OR BREAST FEEDING

If pregnant or breast-feeding, ask a health professional before use.

Keep out of reach of children.

Directions

- adults and children 12 years and over: chew and swallow 1-2 chewable tablets every 2 to 4 hours as symptoms occur, or as directed by a doctor
- children under 12 years: consult a doctor
- do not take more than 6 chewable tablets in a 24-hour period

Other information

- each chewable tablet contains: calcium 330 mg
- store at room temperature. Avoid excessive heat above 40°C (104°F).
- close cap tightly after use

Inactive ingredients

acacia, carmine, carnauba wax, citric acid, corn starch, corn syrup, FD&C red #40 aluminum lake, flavors, hydrogenated coconut oil, hydrogenated vegetable oil, lecithin, maltodextrin, methyl paraben, modified starch, potassium hydroxide, pregelatinized modified starch, propyl paraben, propylene glycol, shellac, sorbic acid, sorbitol, sugar, titanium dioxide, triacetin, water, white wax

Questions?

1-800-986-0369

Dist. by:
Bayer HealthCare LLC
Whippany, NJ 07981

PRINCIPAL DISPLAY PANEL - 32 Tablet Bottle Label

Alka-
Seltzer ®
Calcium Carbonate / Antacid
Simethicone / AntiGas

tropical punch

HEARTBURN+GAS
RELIEFCHEW™

Fast Powerful Relief

BAYER

32 CHEWABLE TABLETS